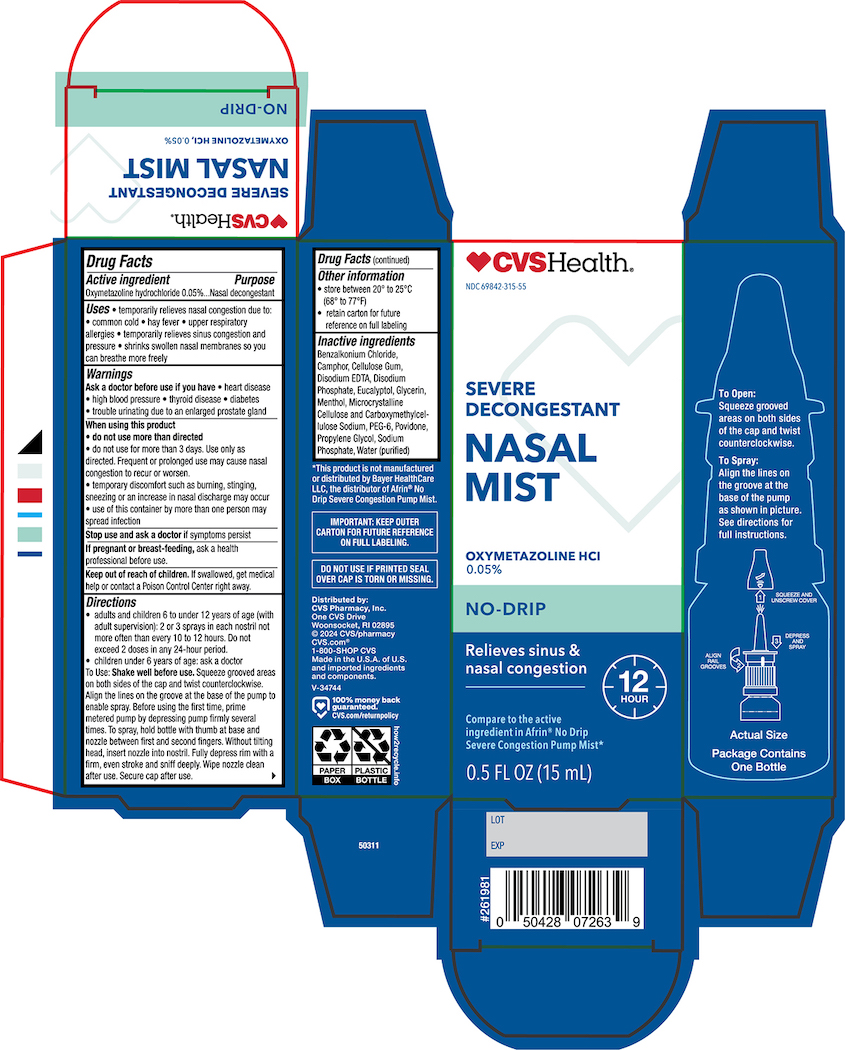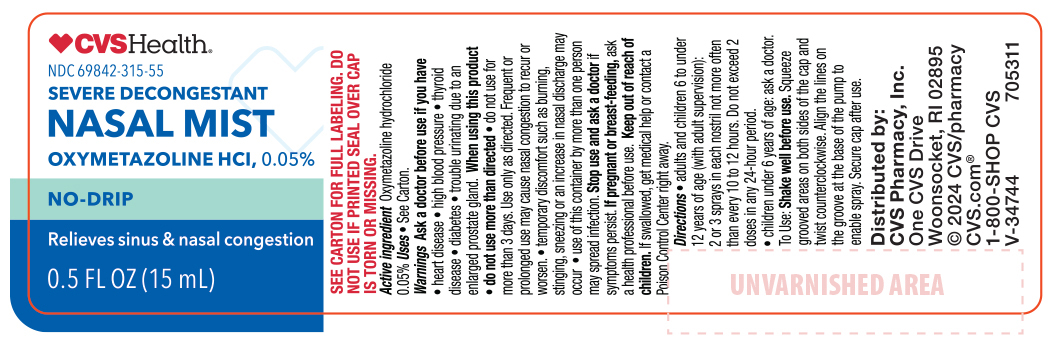 DRUG LABEL: No Drip Severe Nasal Mist
NDC: 69842-315 | Form: LIQUID
Manufacturer: CVS Health
Category: otc | Type: HUMAN OTC DRUG LABEL
Date: 20250926

ACTIVE INGREDIENTS: OXYMETAZOLINE HYDROCHLORIDE 50 mg/100 mL
INACTIVE INGREDIENTS: MICROCRYSTALLINE CELLULOSE; GLYCERIN; POLYETHYLENE GLYCOL 300; EDETATE DISODIUM; SODIUM PHOSPHATE, MONOBASIC; SODIUM PHOSPHATE, DIBASIC; BENZYL ALCOHOL; BENZALKONIUM CHLORIDE; WATER; POVIDONE; CARBOXYMETHYLCELLULOSE SODIUM; CAMPHOR (SYNTHETIC); MENTHOL; EUCALYPTOL

CVS NO DRIP SEVERE NASAL MIST

Drug Facts

Active Ingredient
Oxymetazoline Hydrochloride 0.05%

Purpose

Nasal Decongestant

Uses

Temporarily relieves nasal congestion due to:

- common cold
- hay fever
- upper respiroty allergies
- temporarily relieves sinus congestion and pressure
- Shrinks swollen membranes so you can breathe more freely

Ask a Doctor before use if you have

- heart diease
- high blood pressure
- diabetes
- thyiod diease
- trouble urinating due to enlarged rostate gland.

When using this product

- Do not use more than directed
- do not use for more than three days, Use only as directed. Frequent or prolonged use may cause nasal congestion to recur or worsen.
- temporary discomfort such as burning ,stinging, sneezing or an increase in nasal discharge may occur.
- use of this container by more than one person may spread infection.

stop use and ask a doctor if

symptoms persist.

if pregnant or breast-feeding

ask a health professional before use.

Keep out of the reach of children

if swallowed, get medical help or contact a Poison Control Center right away.

Directions

- Before using for the first time, remove the protective cap form the tip and prime the pump by depressing pump firmly several times. To spray, hold bottle with thumb at base and nozzle between first and second fingers. Without tilting head, insert nozzle into nostrile. Fully depress rim with a firm and even stroke, and sniff deeply.
- Wipe nozzle clean after use.
- Adults and children 6 to under 12 years of age (with adult supervision):2 or 3 sprays in each nostril not more than every 10 to 12 hours. Do not exceed 2 doses in any 24-hour period.
- Children under 6 years of age consult a doctor.

Other information

- store between 20° and 25°C (68° to 77°F)
- retain carton for future reference on full labeling

Inactive Ingredients

Benzalkonium Chloride, Camphor, Cellulose Gum, Disodium EDTA, Disodium Phosphate, Eucalyptol, Glycerin, Menthol, Microcrystalline Cellulose and Carboxymethylcellulose Sodium, PEG-6, Povidone, Propylene Glycol, Sodium Phosphate, Water (purified)

Principal Panel 0.5 FLOZ Bottle

CVS Health Severe Congestant Nasal Mist No Drip

Nasal Spray

Oxymetazoline HCL 0.05%

12 hour Nasal Spray

Net Wt 0.5 FLOZ (15ml)